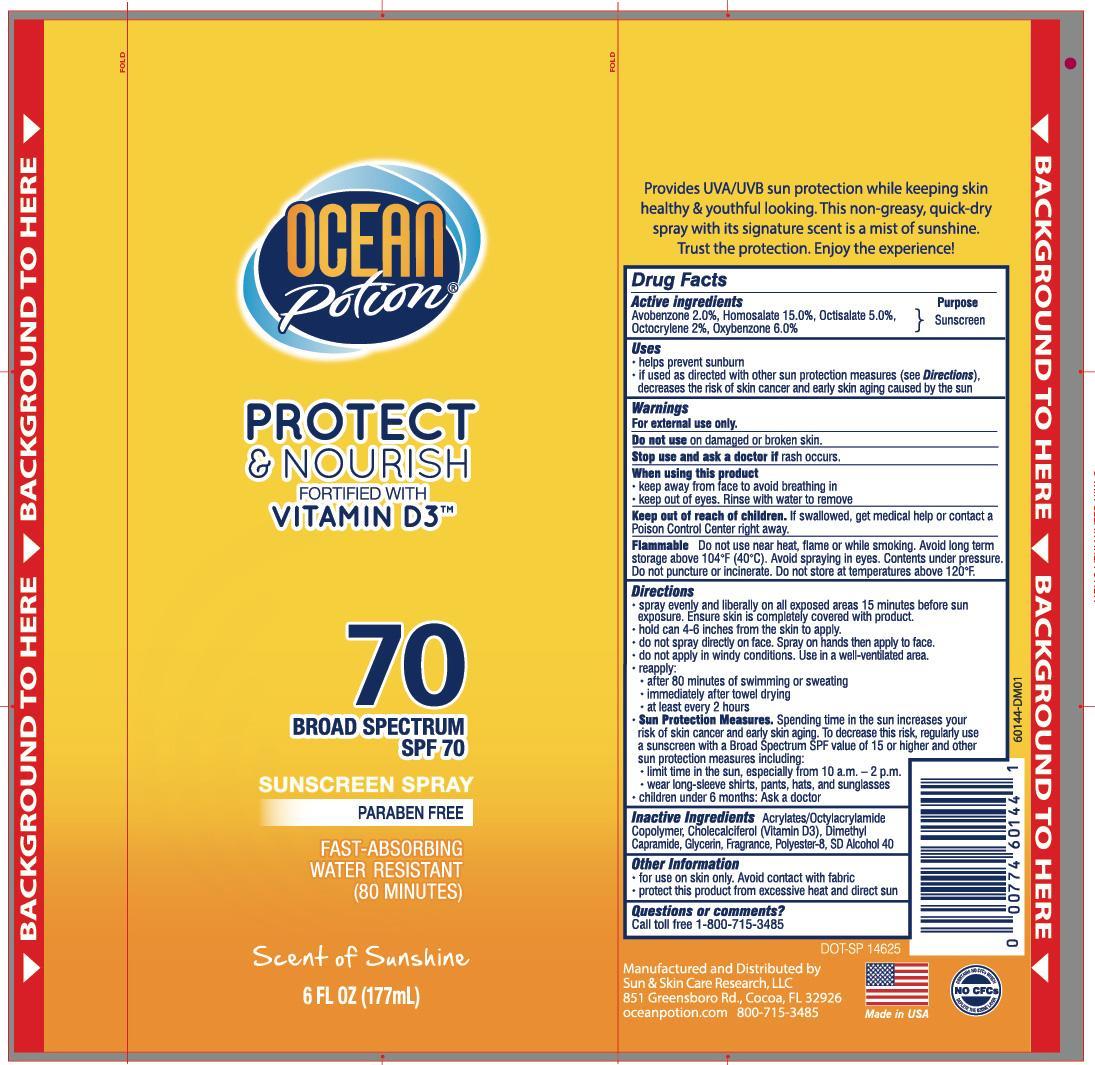 DRUG LABEL: Ocean Potion Instant Dry 70 Mist Sunscreen
NDC: 62802-644 | Form: SPRAY
Manufacturer: Sun & Skin Care Research, LLC
Category: otc | Type: HUMAN OTC DRUG LABEL
Date: 20140718

ACTIVE INGREDIENTS: HOMOSALATE 15 g/100 g; OCTISALATE 5 g/100 g; OCTOCRYLENE 2 g/100 g; AVOBENZONE 2 g/100 g; OXYBENZONE 6 g/100 g
INACTIVE INGREDIENTS: ALCOHOL; CHOLECALCIFEROL; DIMETHYL CAPRAMIDE; GLYCERIN; POLYESTER-8 (1400 MW, CYANODIPHENYLPROPENOYL CAPPED)

Drug Facts

Active Ingredients

- Homosalate: 15%
- Oxybenzone: 6%
- Octisalate: 5%
- Octocrylene: 3%
- Avobenzone: 2%

Purpose

Sunscreen

Uses

- helps prevent sunburn
- If used as directed with other skin protection measures (see Directions), decreases the risk of skin cancer and early skin aging caused by the sun.

Warnings

For external use only. Do not use on damaged or broken skin. Stop use and ask a doctor if rash occurs. When using this product keep away from face to avoid breathing in. Rinse with water to remove. Keep out of the reach of children. If swallowed, get medical help or contact a Poison Control Center right away. Flammable Do not use near heat, flame or while smoking. Avoid long term storage above 104°F (40°C). Avoid spraying in eyes. Contents under pressure. Do not puncture or incinerate. Do not store in temperatures above 120°F.

Directions

- spray evenly and liberally on all exposed areas 15 minutes before sun exposure. Ensure skin is completely covered with product
- hold can 4-6 inches away from the skin to apply
- do not spray directly on face. Spray on hands then apply to face
- do not apply in windy conditions. Use in a well-ventilated area
- reapply after 80 minutes of swimming or sweating and immediately after towel drying
- at least every 2 hours
- Sun Protection Measures. Spending time in the sun increases your risk of skin cancer and early skin aging. To decrease this risk, regularly use a sunscreen with a Broad Spectrum SPF value of 15 or higher and other sun protection measures including limiting time in the sun, especially from 10a.m.-2p.m., wear long-sleeved shirts, pants hats and sunglasses.
- children under 6 months: Ask a doctor

Other Information

- For use on skin only
- Avoid contact with fabric
- Protect this product from excessive heat and direct sun